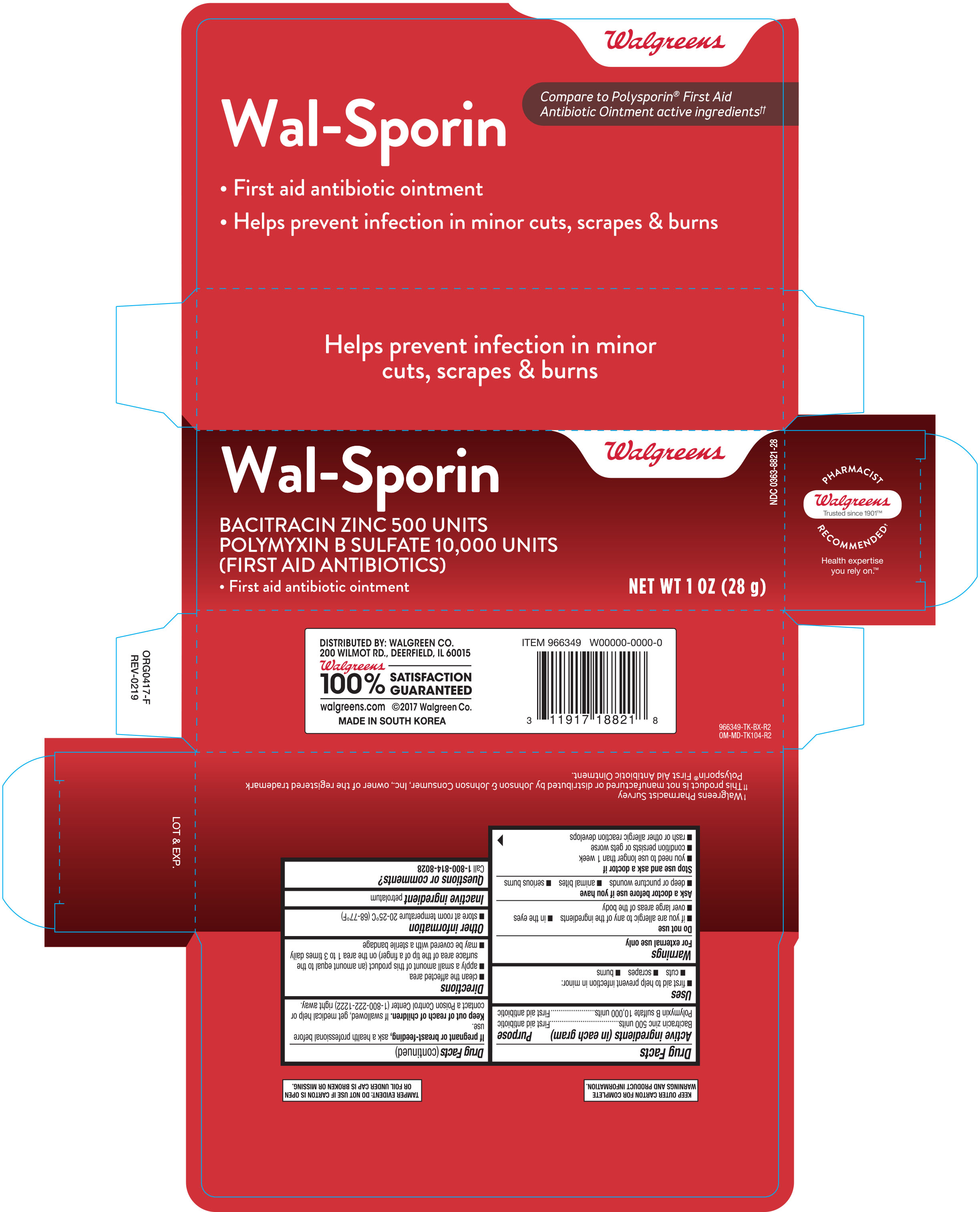 DRUG LABEL: Walgreens Wal-Sporin First Aid Antibiotic
NDC: 0363-8821 | Form: OINTMENT
Manufacturer: Walgreen Co.
Category: otc | Type: HUMAN OTC DRUG LABEL
Date: 20190319

ACTIVE INGREDIENTS: BACITRACIN ZINC 500 [USP'U]/1 g; POLYMYXIN B SULFATE 10000 [USP'U]/1 g
INACTIVE INGREDIENTS: PETROLATUM

Walgreens Wal-Sporin Antibiotic Ointment 1 oz 966349 (2019)

Active ingredients (in each gram) Purpose

Bacitracin zinc 500 units............................................................First aid antibiotic

Polymyxin B 10,000 units..........................................................First aid antibiotic

Uses

- first aid to help prevent infection in minor:
- cuts
- scrapes
- burns

Warnings

For external use only.

Do not use

- if you are allergic to any of the ingredients
- in the eyes
- over large areas of the body

Ask a doctor before use if you have

- deep or puncture wounds
- animal bites
- serious burns

Stop use and ask a doctor if

- you need to use longer than 1 week
- condition persists or gets worse
- rash or other allergic reaction develops

PREGNANCY OR BREAST FEEDING

If pregnant or breast-feeding, ask a health professional before use.

Keep out of reach of children. If swallowed, get medical help or contact a Poison Control Center right away.

Directions

- clean the affected area
- apply a small amount of this product (an amount equal to the surface are of the tip of a finger) on the area 1 to 3 times daily
- may be covered with a sterile bandage

Other information

- store at 20° to 25°C (68° to 77°F)

Inactive ingredients

white petrolatum base

DOSAGE AND ADMINISTRATION

DISTRIBUTED BY: WALGREEN CO.

200 WILMOT RD., DEERFIELD, IL 60015

walgreens.com

MADE IN SOUTH KOREA